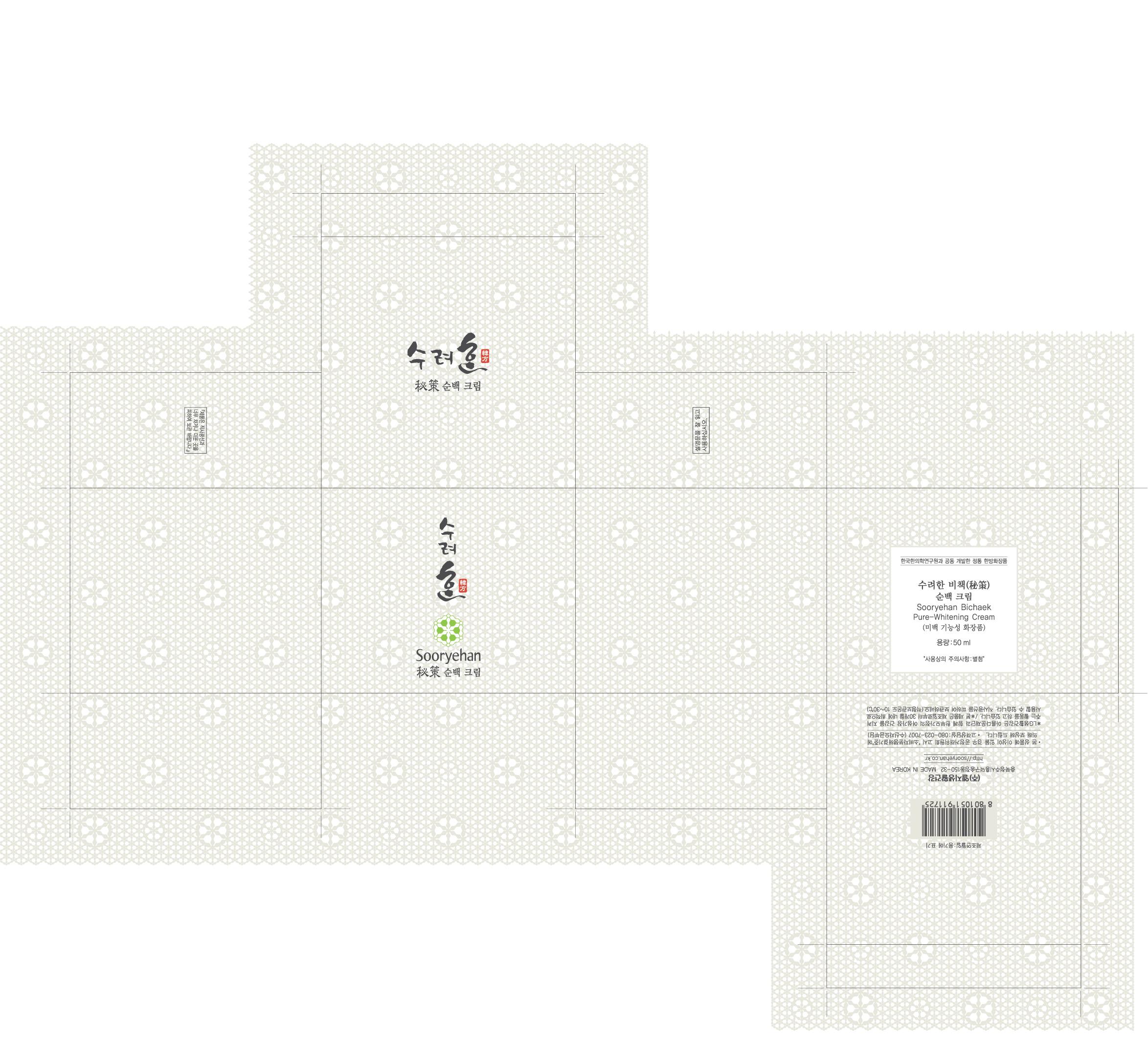 DRUG LABEL: Sooryehan Pure-Whitening 
NDC: 53208-441 | Form: CREAM
Manufacturer: LG Household and Healthcare, Inc.
Category: otc | Type: HUMAN OTC DRUG LABEL
Date: 20100514

ACTIVE INGREDIENTS: Polydatin 0.22 mL/100 mL
INACTIVE INGREDIENTS: WATER; DIPROPYLENE GLYCOL; GLYCERIN; CAPRIC ACID; CYCLOMETHICONE 5; ALCOHOL; GLYCERYL MONOSTEARATE; TROLAMINE; CARBOMER 934; METHYLPARABEN; DIMETHICONE; ETHYLPARABEN; EDETATE TRISODIUM; FD&C YELLOW NO. 6; FD&C YELLOW NO. 5

DRUG FACTS

ACTIVE INGREDIENT

Polydatin 0.22mL/100mL

Keep out of reach of children. Is swallowed, get medical help or contact a Poison Control Center right away.

Keep out of reach of children. Is swallowed, get medical help or contact a Poison Control Center right away.

WHEN USING

Keep out of eyes. Rinse with water to remove.

PACKAGE LABEL

Sooryehan